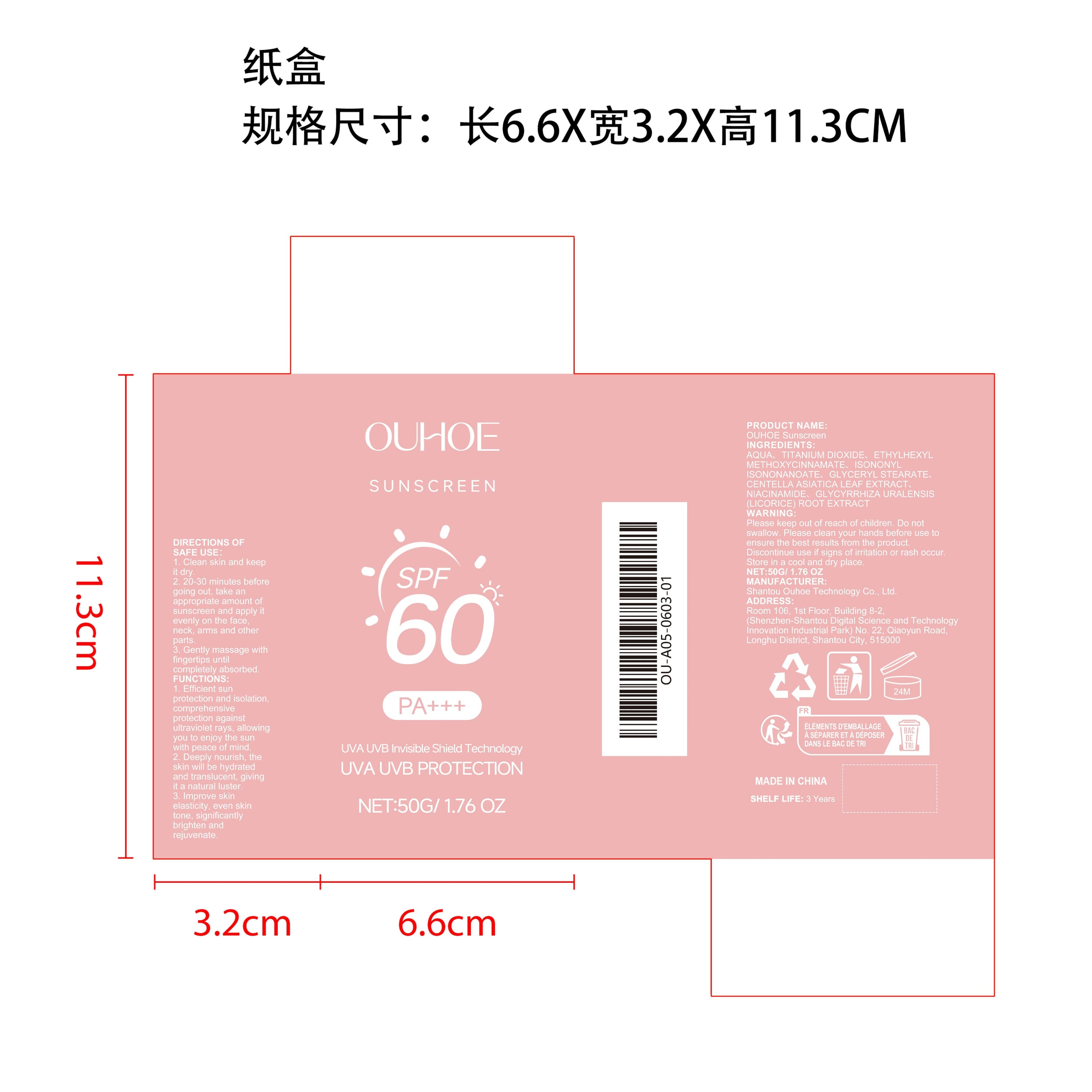 DRUG LABEL: OUHOE Sunscreen
NDC: 85163-010 | Form: CREAM
Manufacturer: Shantou Ouhoe Technology Co., Ltd.
Category: otc | Type: HUMAN OTC DRUG LABEL
Date: 20251127

ACTIVE INGREDIENTS: CENTELLA ASIATICA LEAF 0.01 mg/50 mg; GLYCYRRHIZA URALENSIS ROOT 0.01 mg/50 mg
INACTIVE INGREDIENTS: NIACINAMIDE 0.01 mg/50 mg; AQUA 29.97 mg/50 mg; TITANIUM DIOXIDE 12.5 mg/50 mg; ISONONYL ISONONANOATE 2 mg/50 mg; ETHYLHEXYL METHOXYCINNAMATE 4.5 mg/50 mg; GLYCERYL STEARATE 1 mg/50 mg

ACTIVE INGREDIENT

CENTELLA ASIATICA LEAF EXTRACT、GLYCYRRHIZA URALENSIS (LICORICE) ROOT EXTRACT

PURPOSE

1. Efficient sun protection and isolation, comprehensive protection against ultraviolet rays, allowing you to enjoy the sun with peace of mind.

2. Deeply nourish, the skin will be hydrated and translucent, giving it a natural luster.

3. Improve skin elasticity, even skin tone, significantly brighten and rejuvenate.

WHEN USING

1. Clean skin and keep it dry.

2. 20-30 minutes before going out, take an appropriate amount of sunscreen and apply it evenly on the face, neck, arms and other parts.

3. Gently massage with fingertips until completely absorbed.

WARNINGS

Please keep out of reach of children. Do not swallow.Please clean your hands before use to ensure the best results from the product. Discontinue use if signs of irritation or rash occur. Store in a cool and dry place.

STOP USE

Discontinue use if signs of irritation or rash occur.

STOP USE

Discontinue use if signs of irritation or rash occur.

KEEP OUT OF REACH OF CHILDREN

Please keep out of reach of children. Do not swallow.

STORAGE AND HANDLING

Store in a cool and dry place.

INACTIVE INGREDIENT

AQUA、TITANIUM DIOXIDE、ETHYLHEXYL METHOXYCINNAMATE、ISONONYL ISONONANOATE、GLYCERYL STEARATE、NIACINAMIDET

INDICATIONS AND USAGE

1. Clean skin and keep it dry.

2. 20-30 minutes before going out, take an appropriate amount of sunscreen and apply it evenly on the face, neck, arms and other parts.

3. Gently massage with fingertips until completely absorbed.

DOSAGE AND ADMINISTRATION

1. Clean skin and keep it dry.

2. 20-30 minutes before going out, take an appropriate amount of sunscreen and apply it evenly on the face, neck, arms and other parts.

3. Gently massage with fingertips until completely absorbed.